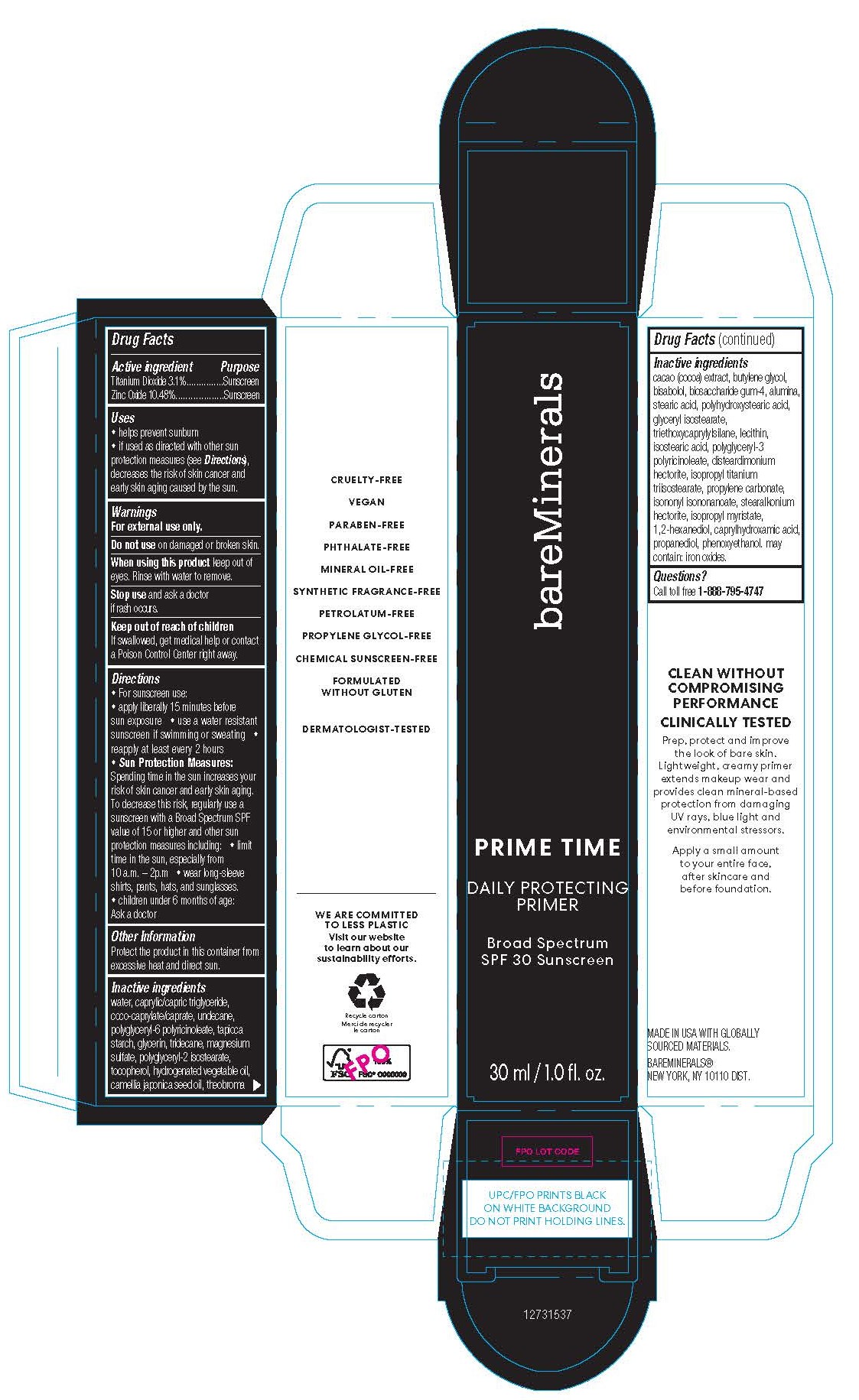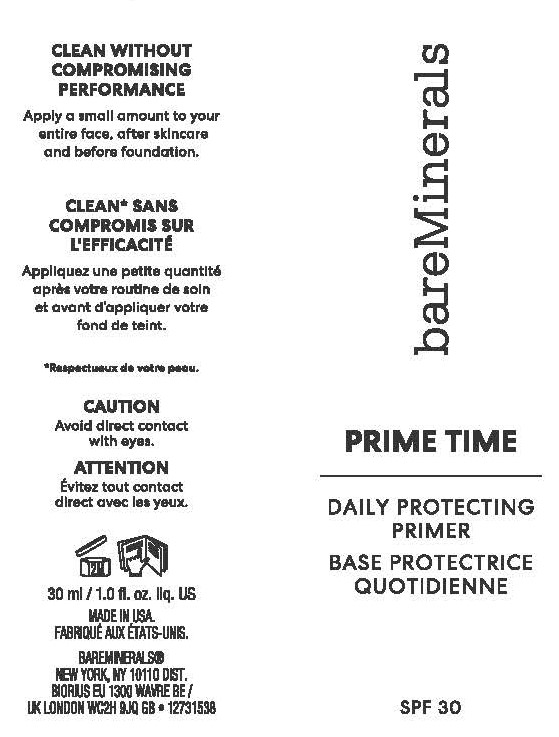 DRUG LABEL: Prime Time Daily Protecting Primer SPF 30
NDC: 51514-0364 | Form: LOTION
Manufacturer: Autumn Harp Inc.
Category: otc | Type: HUMAN OTC DRUG LABEL
Date: 20240103

ACTIVE INGREDIENTS: ZINC OXIDE 10.49 g/100 g; TITANIUM DIOXIDE 3.13 g/100 g
INACTIVE INGREDIENTS: MEDIUM-CHAIN TRIGLYCERIDES; TOCOPHEROL; FERRIC OXIDE RED; ISOPROPYL TITANIUM TRIISOSTEARATE; COCO-CAPRYLATE/CAPRATE; UNDECANE; POLYGLYCERYL-6 POLYRICINOLEATE; STARCH, TAPIOCA; TRIDECANE; STEARIC ACID; WATER; GLYCERIN; MAGNESIUM SULFATE ANHYDROUS; 1,2-HEXANEDIOL; THEOBROMA CACAO WHOLE; CAPRYLHYDROXAMIC ACID; LECITHIN, SUNFLOWER; POLYGLYCERYL-3 PENTARICINOLEATE; TRIETHOXYCAPRYLYLSILANE; GLYCERYL ISOSTEARATE; POLYHYDROXYSTEARIC ACID (2300 MW); .ALPHA.-BISABOLOL, (+)-; FERRIC OXIDE YELLOW; POLYGLYCERYL-2 ISOSTEARATE; BUTYLENE GLYCOL; ISOPROPYL MYRISTATE; ISOSTEARIC ACID; BIOSACCHARIDE GUM-4; PROPYLENE CARBONATE; HYDROGENATED PALM KERNEL OIL; PHENOXYETHANOL; DISTEARDIMONIUM HECTORITE; PROPANEDIOL; ALUMINUM OXIDE; ISONONYL ISONONANOATE; CAMELLIA JAPONICA SEED OIL; .ALPHA.-TOCOPHEROL; STEARALKONIUM HECTORITE

Prime Time Daily Protecting Primer SPF 30

Active Ingredients

Titanium Dioxide 3.1%

Zinc Oxide 10.49%

INDICATIONS AND USAGE

Sunscreen

Sunscreen

Uses

- helps prevent sunburn
- if used as directed with other sun protection measures (see Directions), decreases the risk of skin cancer and early skin aging caused by the sun.

Warnings

For external use only.

Do not use on damaged or broken skin.

When using this product keep out of eyes. Rinse with water to remove.

Stop use and ask a doctor if rash occurs.

Keep out of reach of children

If swallowed, get medical help or contact a Poison Control Center right away.

Directions

- For sunscreen use:
- apply liberally 15 minutes before sun exposure
- use a water resistant sunscreen if swimming or sweating
- reapply at least every 2 hours
- Sun Protection Measures:

Spending time in the sun increases your risk of skin cancer and early skin aging. To decrease this risk, regularly use a sunscreen with a Broad Spectrum SPF value of 15 or higher and other sun protection measures including:

- limit time in the sun, especially from 10 am - 2 pm
- wear long sleeve shirts, pants, hats and sunglasses
- children under 6 months of age: Ask a doctor

Other Information

Protect this product in this container from excessive heat and direct sun.

Inactive Ingredients

Water, Caprylic/Capric Triglyceride, Coco-Caprylate/Caprate, Undecane, Polyglyceryl-6 Polyricinoleate, Tapioca Starch, Glycerin, Tridecane, Magnesium Sulfate, Polyglyceryl-2 Isostearate, Tocopherol, Hydrogenated Vegetable Oil, Phenoxyethanol, Glyceryl Isostearate, Disteardimonium Hectorite, Polyhydroxystearic Acid, Propanediol, Bisabolol, Stearic Acid, Iron Oxide (CI 77492), Alumina, 1,2-Hexanediol, Isononyl Isononanoate, Camellia Japonica Seed Oil, Theobroma Cacao (Cocoa) Extract, Butylene Glycol, Isopropyl Myristate, Isostearic Acid, Iron Oxides (CI 77491), Caprylhydroxamic Acid, Lecithin, Polyglyceryl-3 Polyricinoleate, Triethoxycaprylylsilane, Biosaccharide gum-4, Isopropyl Titanium Triisostearate, Stearalkonium Hectorite, Propylene Carbonate.

Questions?

Call toll free 1-888-795-4747

Principle Display Panel

Image Content